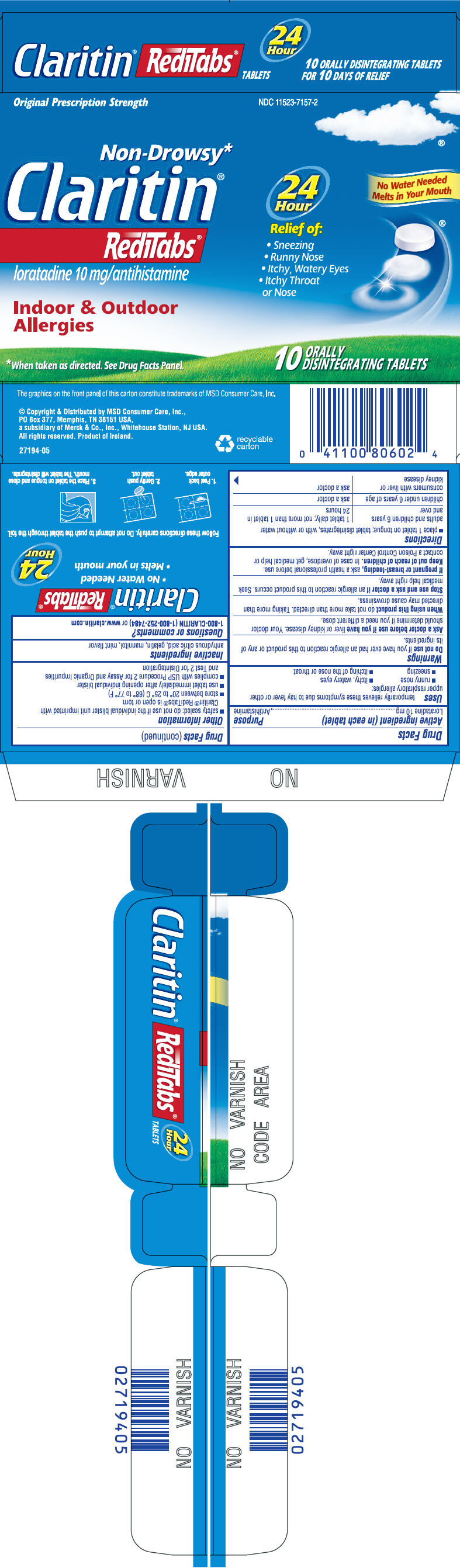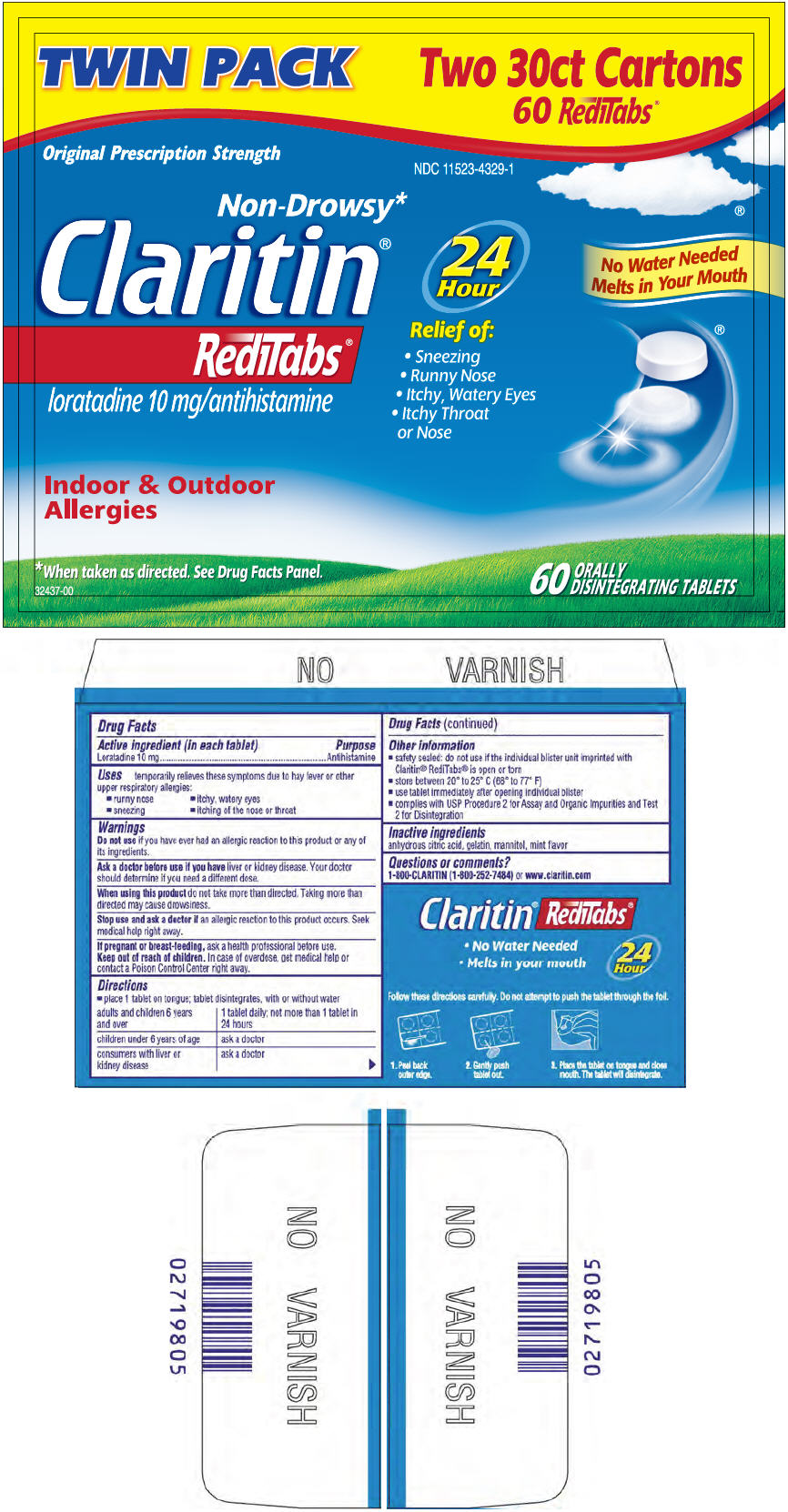 DRUG LABEL: Claritin
NDC: 11523-7157 | Form: TABLET, ORALLY DISINTEGRATING
Manufacturer: Bayer Healthcare LLC.
Category: otc | Type: HUMAN OTC DRUG LABEL
Date: 20251205

ACTIVE INGREDIENTS: LORATADINE 10 mg/1 1
INACTIVE INGREDIENTS: MANNITOL; ANHYDROUS CITRIC ACID; GELATIN

Claritin®
RediTabs®

Drug Facts

Active ingredient (in each tablet)

Loratadine 10 mg

Purpose

Antihistamine

Uses

temporarily relieves these symptoms due to hay fever or other upper respiratory allergies:

- runny nose
- itchy, watery eyes
- sneezing
- itching of the nose or throat

Warnings

Do not use if you have ever had an allergic reaction to this product or any of its ingredients.

Ask a doctor before use if you have liver or kidney disease. Your doctor should determine if you need a different dose.

When using this product do not take more than directed. Taking more than directed may cause drowsiness.

Stop use and ask a doctor if an allergic reaction to this product occurs. Seek medical help right away.

PREGNANCY OR BREAST FEEDING

If pregnant or breast-feeding, ask a health professional before use.

Keep out of reach of children. In case of overdose, get medical help or contact a Poison Control Center right away.

Directions

- place 1 tablet on tongue; tablet disintegrates, with or without water

adults and children 6 years and over | 1 tablet daily; not more than 1 tablet in 24 hours
children under 6 years of age | ask a doctor
consumers with liver or kidney disease | ask a doctor

Other information

- safety sealed: do not use if the individual blister unit imprinted with Claritin® RediTabs® is open or torn
- store between 20° to 25°C (68° to 77°F)
- use tablet immediately after opening individual blister
- complies with USP Procedure 2 for Assay and Organic Impurities and Test 2 for Disintegration

Inactive ingredients

anhydrous citric acid, gelatin, mannitol, mint flavor

Questions or comments?

1-800-CLARITIN (1-800-252-7484) or www.claritin.com

Distributed by MSD Consumer Care, Inc.,
PO Box 377, Memphis, TN 38151 USA,
a subsidiary of Merck & Co., Inc., Whitehouse Station, NJ USA.

PRINCIPAL DISPLAY PANEL - 10 Tablet Carton

Original Prescription Strength
NDC 11523-7157-2

Non-Drowsy*
Claritin ®
RediTabs®
loratadine 10 mg/antihistamine

Indoor & Outdoor
Allergies

*When taken as directed. See Drug Facts Panel.

24
Hour

Relief of:

- Sneezing
- Runny Nose
- Itchy, Watery Eyes
- Itchy Throat
  or Nose

No Water Needed
Melts in Your Mouth

10
ORALLY
DISINTEGRATING TABLETS

PRINCIPAL DISPLAY PANEL - 60 Tablet Twin Pack Carton

TWIN PACK

Two 30ct Cartons
60 RediTabs ®

Original Prescription Strength

NDC 11523-4329-1

Non-Drowsy*
Claritin ®
RediTabs®
loratadine 10 mg/antihistamine

Indoor & Outdoor
Allergies

*When taken as directed. See Drug Facts Panel.

24
Hour

Relief of:

- Sneezing
- Runny Nose
- Itchy, Watery Eyes
- Itchy Throat
  or Nose

No Water Needed
Melts in Your Mouth

60
ORALLY
DISINTEGRATING TABLETS